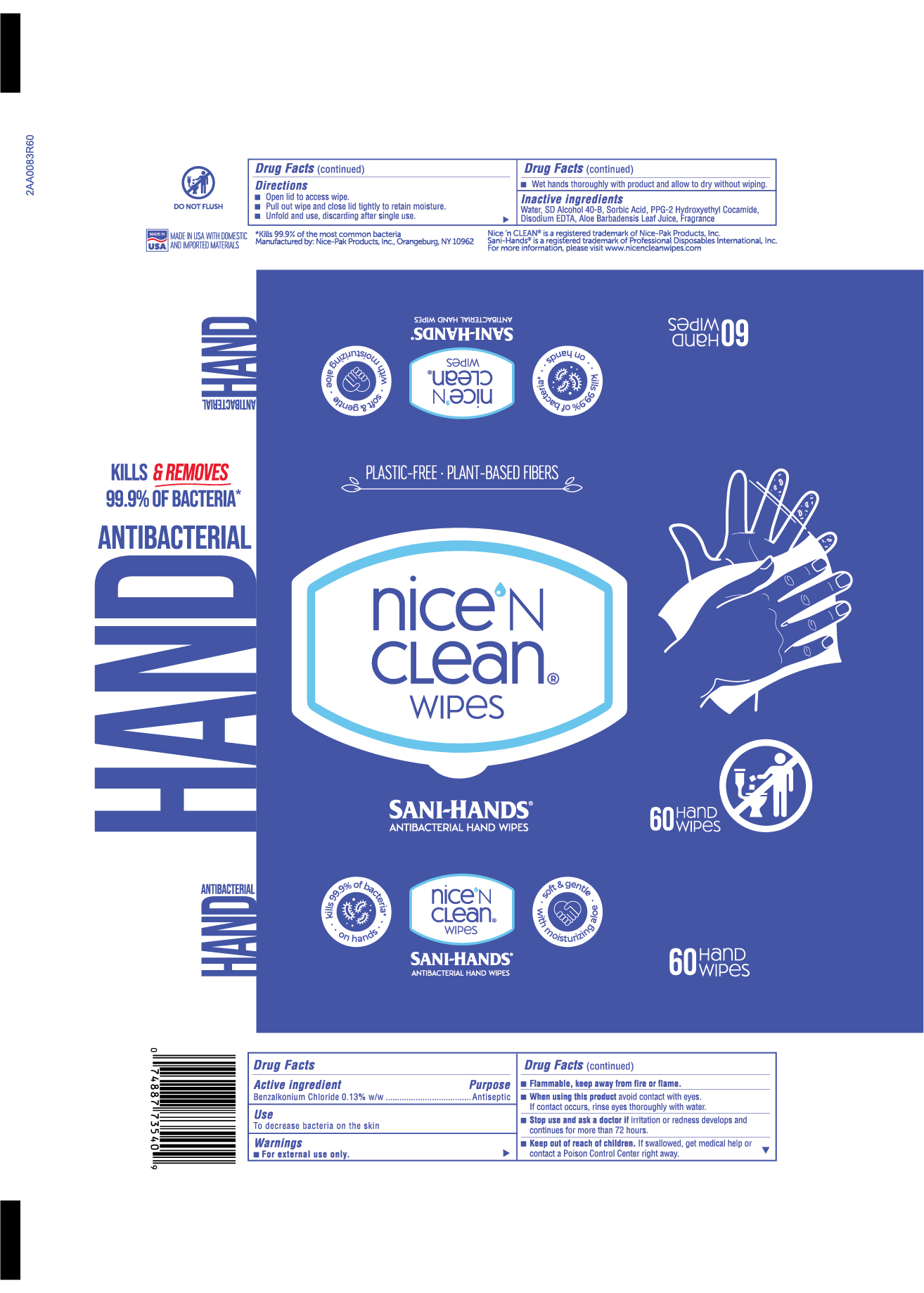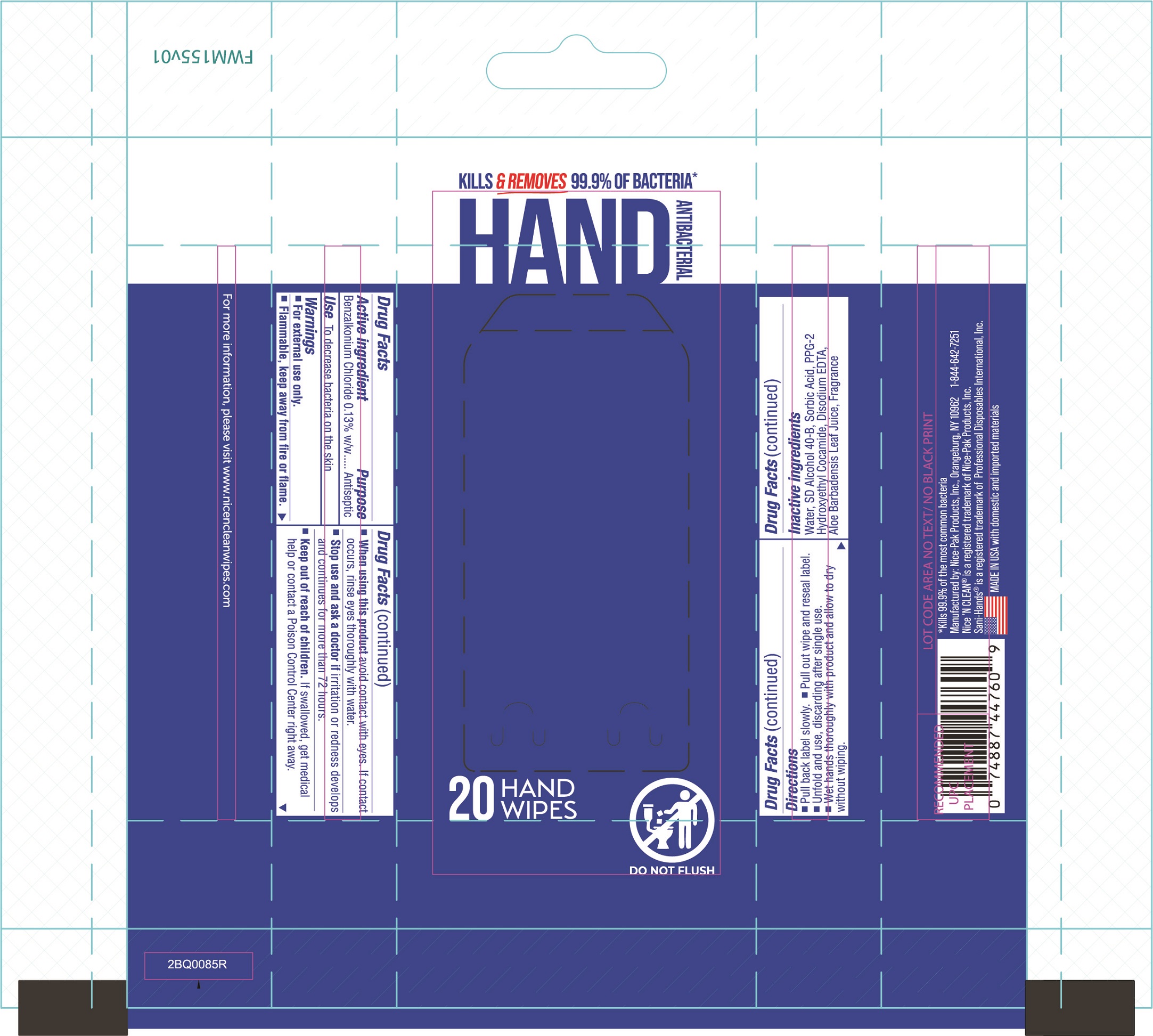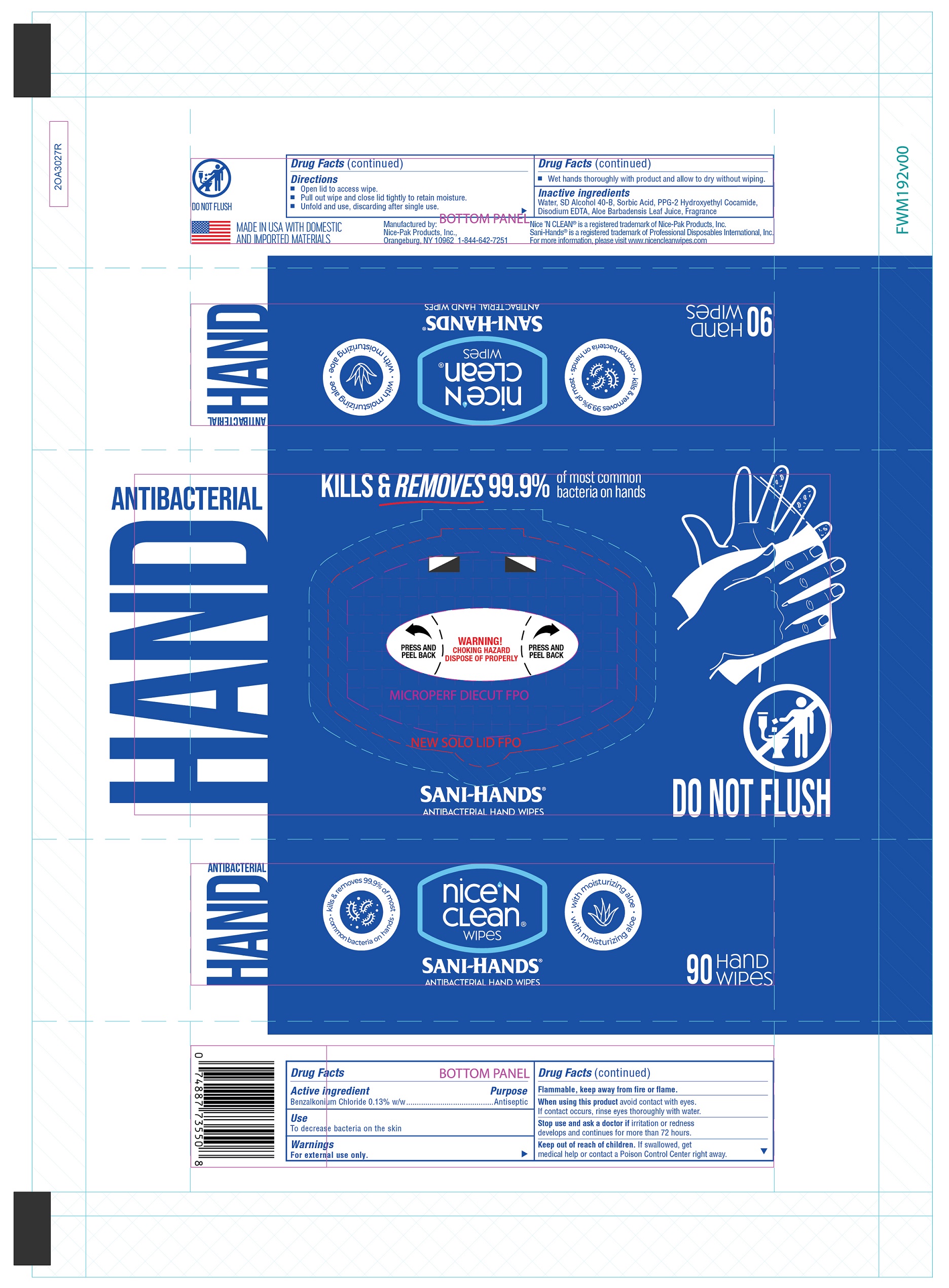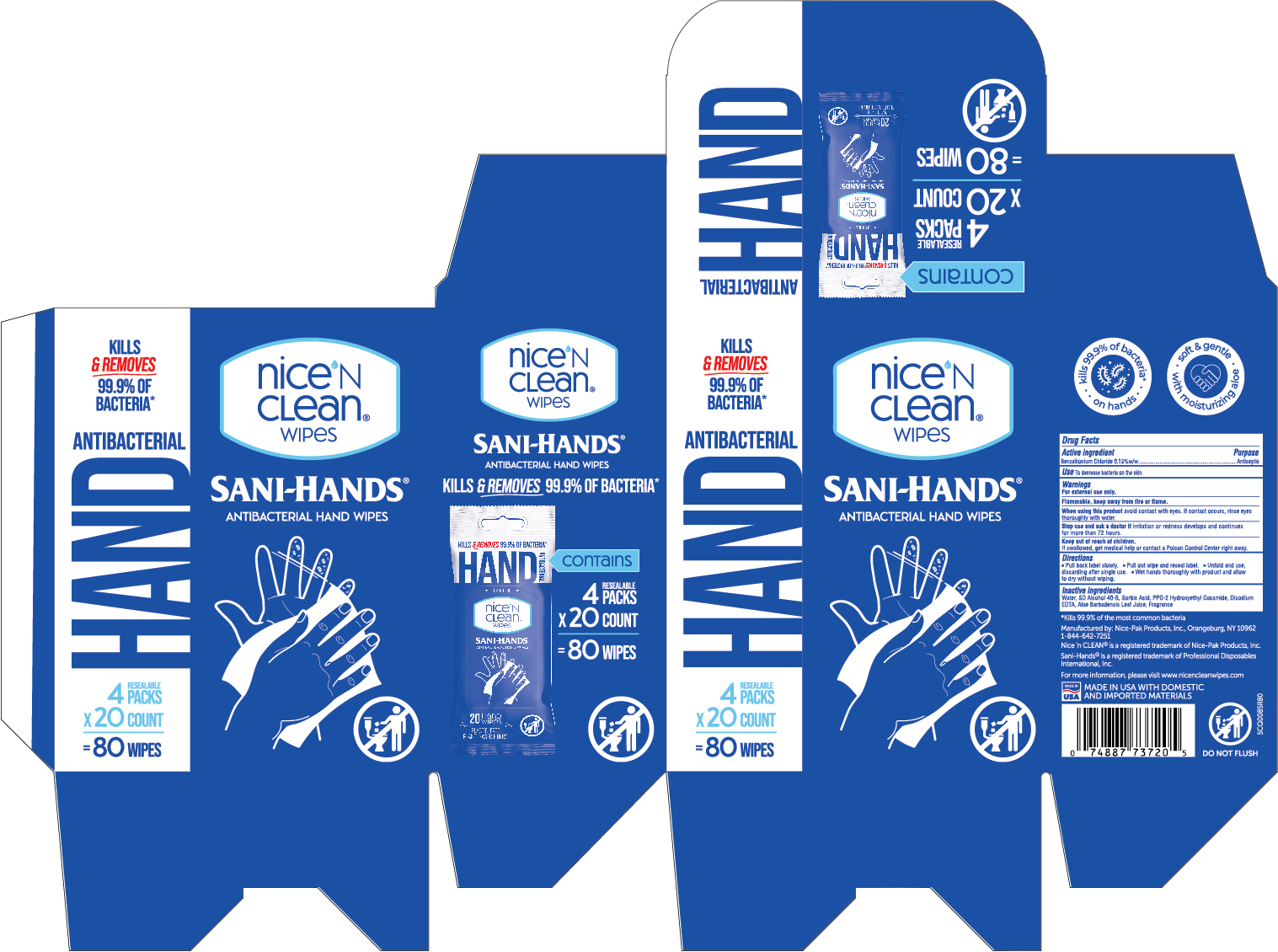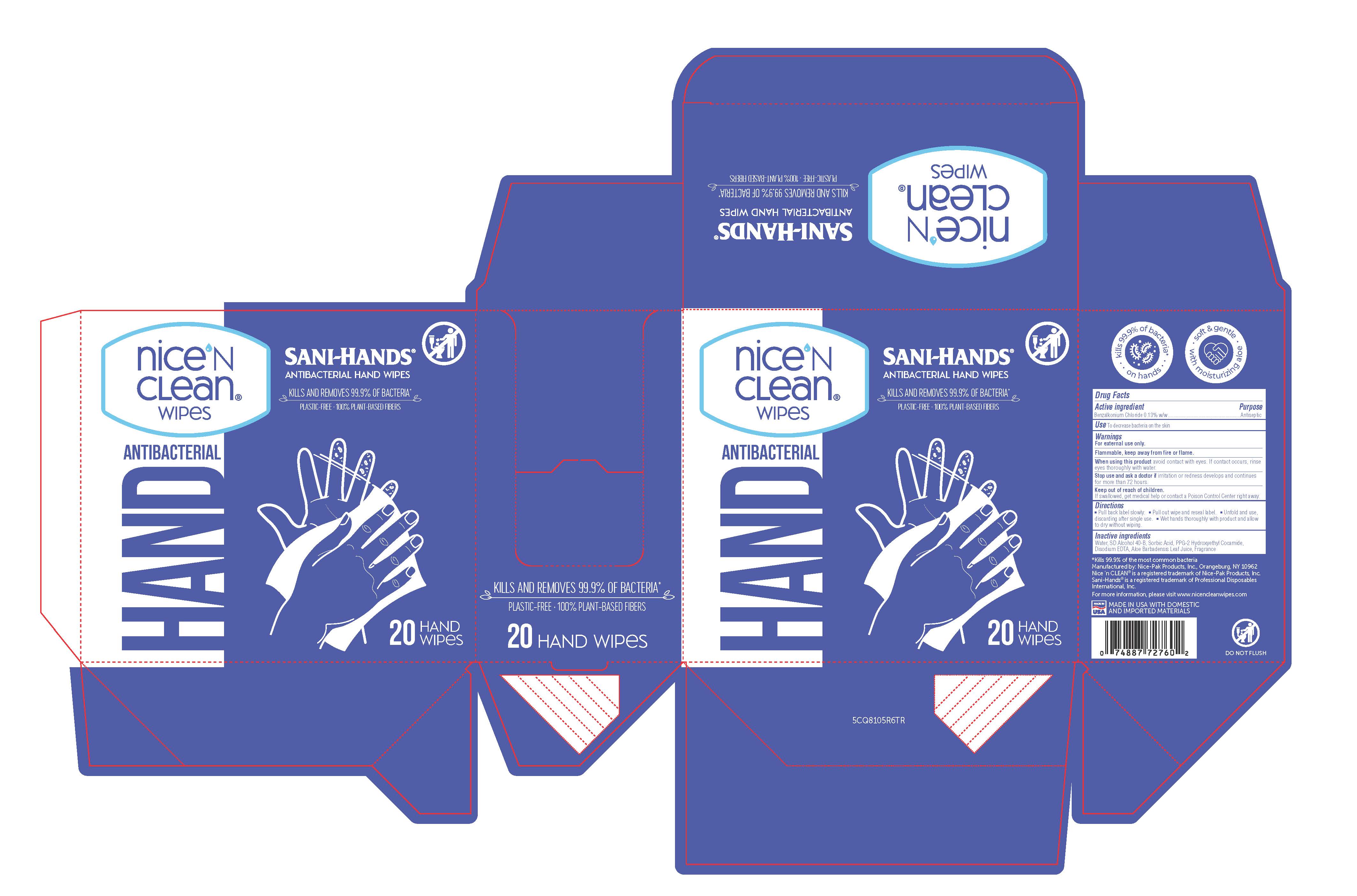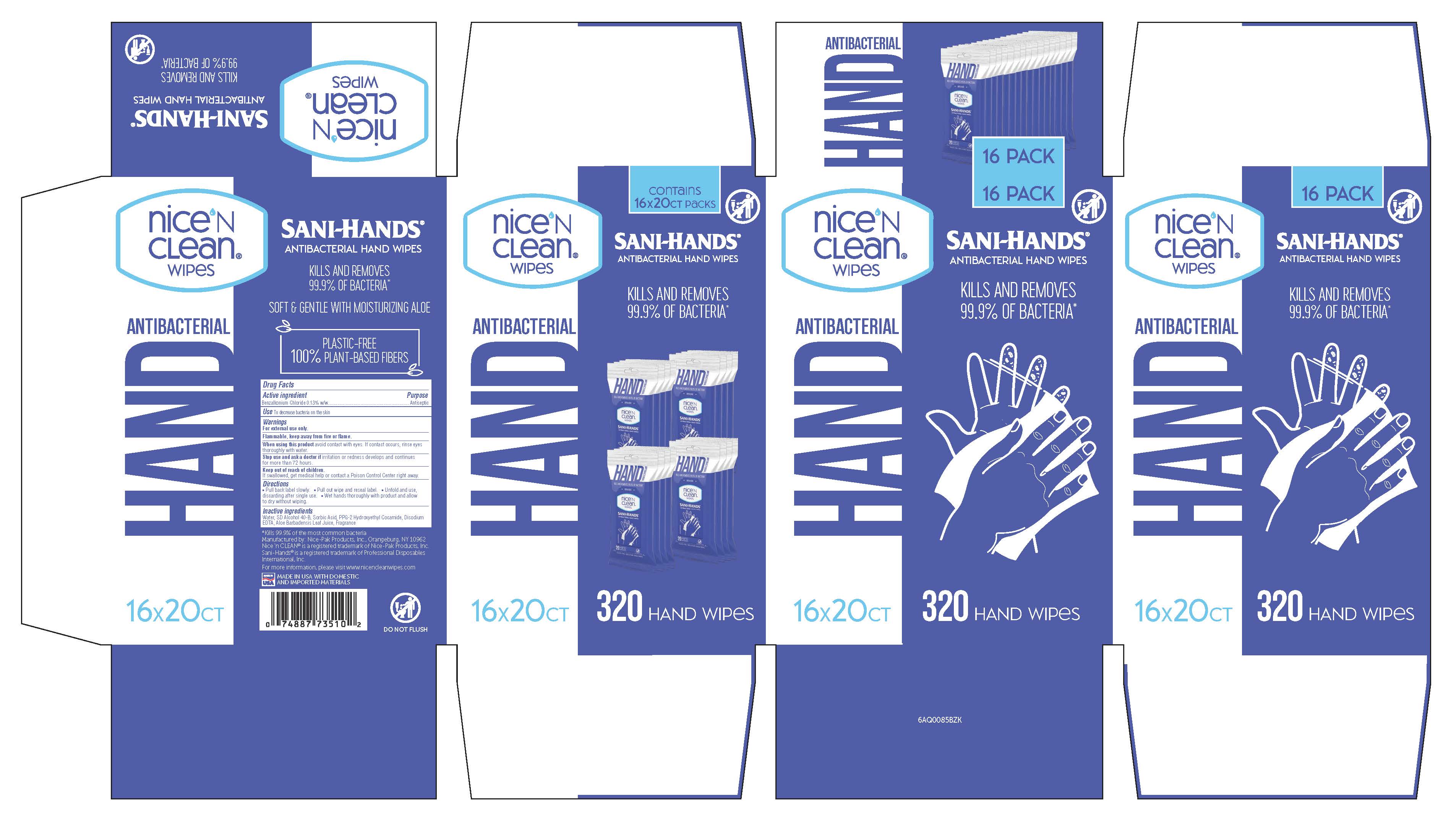 DRUG LABEL: Nice n Clean Wipes Sani-Hands Antibacterial Hand Wipes
NDC: 44385-7014 | Form: SWAB
Manufacturer: Nice-Pak Products, Inc.
Category: otc | Type: HUMAN OTC DRUG LABEL
Date: 20241107

ACTIVE INGREDIENTS: BENZALKONIUM CHLORIDE 0.13 mg/1 mL
INACTIVE INGREDIENTS: ALOE VERA LEAF; EDETATE DISODIUM ANHYDROUS; PPG-2 HYDROXYETHYL COCAMIDE; WATER; ALCOHOL; SORBIC ACID

NICE 'N CLEAN WIPES SANI-HANDS ANTIBACTERIAL HAND WIPES

Active ingredient

Benzalkonium Chloride 0.13%w/w

Purpose

Antiseptic

Use

To decrease bacteria on the skin

Warnings

For external use only.

Flammable, keep away from fire or flame

When using this product avoid contact with eyes. If contact occurs, rinse eyes thoroughly with water.

Stop use and ask a doctor if irritation or redness develolps and contines for more than 72 hours.

Keep out of reach of children.

If swallowed, get medical help or contact a Poison Control Center right away.

Directions

Pull back label slowly.

Pull out wipe and reseal label.

Unfold and use, discarding after single use.

Wet hands thoroughly with product and allow to dry without wiping..

Inactive ingredients

Water, SD Alcohol 40-B, Sorbic Acid, PPG-2 Hydroxyethyl Cocamide, Disodium EDTA, Aloe Barbadensis Leaf Juice, Fragrance

Other information:

For more information, please visit www.nicencleanwipes.com

Keep out of reach of children. If swallowed, get medical

help or contact a Poison Control Center right away.

PACKAGE LABEL

NICE 'N CLEAN WIPES

SANI-HANDS

ANTIBACTERIAL HAND WIPES

HAND ANTIBACTERIAL

KILLS AND REMOVES 99.9% OF BACTERIA*

DO NOT FLUSH

PLASTIC-FREE - 100% PLANT-BASED FIBERS

*KILLS 99.9% OF THE MOST COMMON BACTERIA

MANUFACTURED BY: NICE-PAK PRODUCTS, INC. ORANGEBURG, NY 10962

NICE 'N clean(R) is a registered trademark of Nice-Pak Products, Inc.

Sani-Hands(R) is a registered trademark of Professional Disposables International, Inc.

MADE IN USA with domestic and imported materials

PLASTIC-FREE MADE WITH PLANT-BASED FIBERS

20 count web:

60 count web:

90 Count web:

80 count (4x20ct) in box

320 count (16x20ct) box